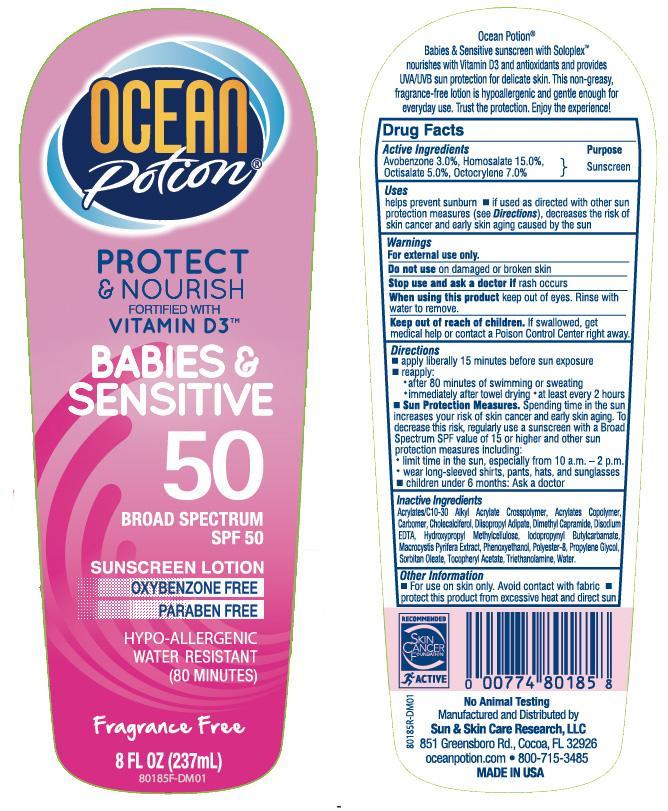 DRUG LABEL: Ocean Potion Gentle and Sensitive 50 Sunscreen
NDC: 62802-182 | Form: LOTION
Manufacturer: Sun & Skin Care Research, LLC
Category: otc | Type: HUMAN OTC DRUG LABEL
Date: 20140718

ACTIVE INGREDIENTS: HOMOSALATE 15 g/100 g; OCTISALATE 5 g/100 g; OCTOCRYLENE 7 g/100 g; AVOBENZONE 3 g/100 g
INACTIVE INGREDIENTS: WATER; CARBOMER COPOLYMER TYPE A (ALLYL PENTAERYTHRITOL CROSSLINKED); CAPRYLYL GLYCOL; CARBOMER HOMOPOLYMER TYPE C; CHOLECALCIFEROL; DIISOPROPYL ADIPATE; DIMETHYL CAPRAMIDE    ; EDETATE DISODIUM; HYPROMELLOSE 2208 (15000 MPA.S); PHENOXYETHANOL; POLYESTER-8 (1400 MW, CYANODIPHENYLPROPENOYL CAPPED); PROPYLENE GLYCOL; SORBITAN MONOOLEATE; ALPHA-TOCOPHEROL ACETATE; TROLAMINE

Drug Facts

Active Ingredients

- Homosalate: 15%
- Octisalate: 5%
- Octocrylene: 7%
- Avobenzone: 3%

Purpose

Sunscreen

Uses

- helps prevent sunburn
- If used as directed with other skin protection measures (see Directions), decreases the risk of skin cancer and early skin aging caused by the sun.

Warnings

For external use only. Do not use on damaged or broken skin. Stop use and ask a doctor if rash occurs. When using this product keep out of eyes. Rinse with water to remove. Keep out of the reach of children. If swallowed, get medical help or contact a Poison Control Center right away.

Directions

- apply liberally 15 minutes before sun exposure
- reapply after 80 minutes of swimming or sweating and immediately after towel drying
- at least every 2 hours
- Sun Protection Measures. Spending time in the sun increases your risk of skin cancer and early skin aging. To decrease this risk, regularly use a sunscreen with a Broad Spectrum SPF value of 15 or higher and other sun protection measures including limiting time in the sun, especially from 10a.m.-2p.m., wear long-sleeved shirts, pants hats and sunglasses.
- children under 6 months: Ask a doctor

Other Information

- For use on skin only
- Avoid contact with fabric
- Protect this product from excessive heat and direct sun